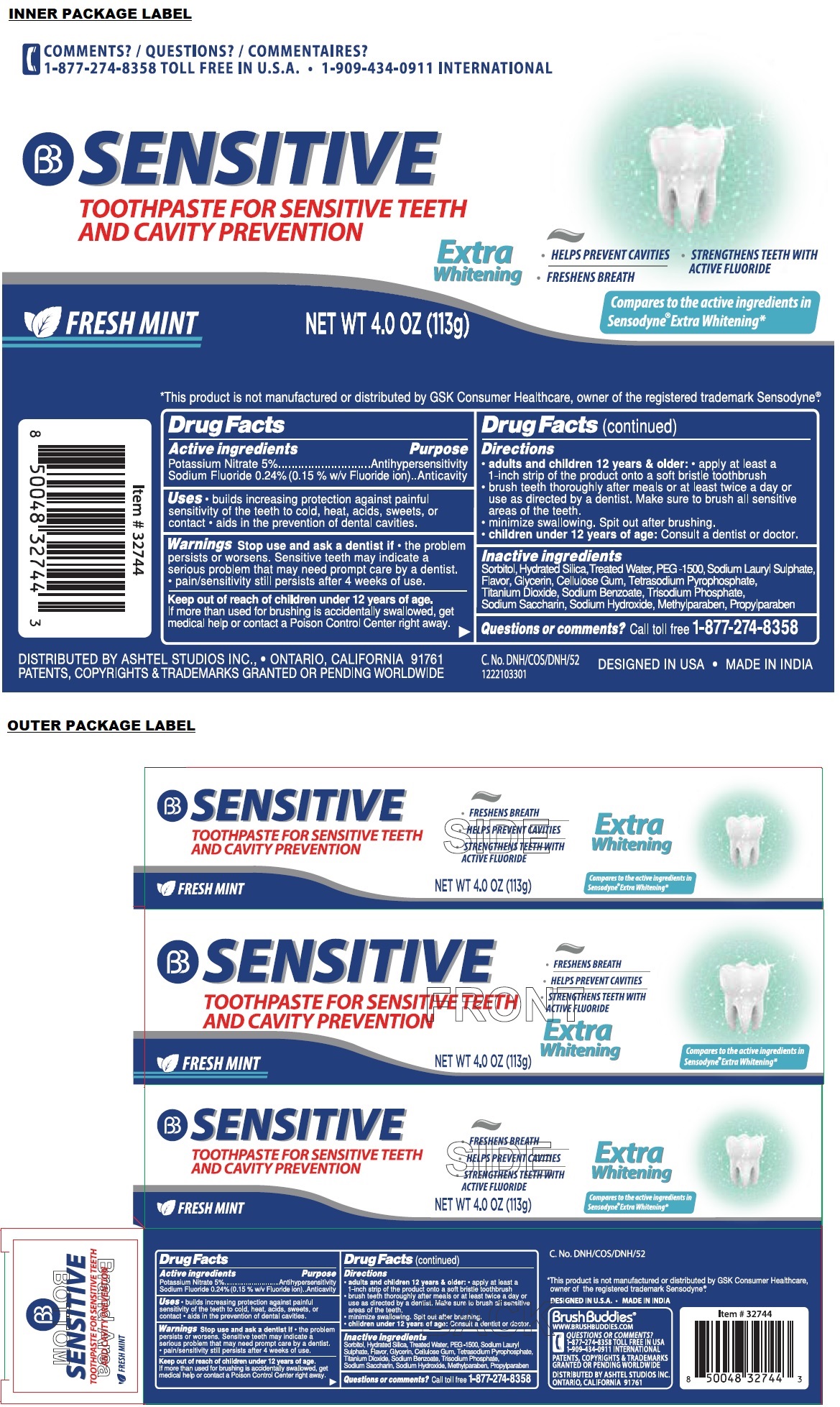 DRUG LABEL: Brush Buddies SENSITIVE Extra Whitening
NDC: 70108-079 | Form: PASTE, DENTIFRICE
Manufacturer: Ashtel Studios, Inc.
Category: otc | Type: HUMAN OTC DRUG LABEL
Date: 20230926

ACTIVE INGREDIENTS: POTASSIUM NITRATE 5 g/100 g; SODIUM FLUORIDE 0.24 g/100 g
INACTIVE INGREDIENTS: SORBITOL; HYDRATED SILICA; WATER; POLYETHYLENE GLYCOL 1600; SODIUM LAURYL SULFATE; GLYCERIN; CARBOXYMETHYLCELLULOSE SODIUM, UNSPECIFIED; SODIUM PYROPHOSPHATE; TITANIUM DIOXIDE; SODIUM BENZOATE; SODIUM PHOSPHATE, TRIBASIC, ANHYDROUS; SACCHARIN SODIUM; SODIUM HYDROXIDE; METHYLPARABEN; PROPYLPARABEN

BB SENSITIVE TOOTHPASTE FOR SENSITIVE TEETH AND CAVITY PREVENTION

Active ingredients

Potassium Nitrate 5%
Sodium Fluoride 0.24% (0.15 % w/v Fluoride ion)

Purpose

Antihypersensitivity
Anticavity

Uses

• builds increasing protection against painful sensitivity of the teeth to cold, heat, acids, sweets, or contact • aids in the prevention of dental cavities.

Warnings

Stop use and ask a dentist if • the problem persists or worsens. Sensitive teeth may indicate a serious problem that may need prompt care by a dentist. • pain/sensitivity still persists after 4 weeks of use.

Keep out of reach of children under 12 years of age.
If more than used for brushing is accidentally swallowed, get medical help or contact a Poison Control Center right away.

Directions

• adults and children 12 years & older: • apply at least a 1-inch strip of the product onto a soft bristle toothbrush
• brush teeth thoroughly after meals or at least twice a day or use as directed by a dentist. Make sure to brush all sensitive areas of the teeth.
• minimize swallowing. Spit out after brushing.
• children under 12 years of age: Consult a dentist or doctor.

Inactive ingredients

Sorbitol, Hydrated Silica, Treated Water, PEG-1500, Sodium Lauryl Sulphate, Flavor, Glycerin, Cellulose Gum, Tetrasodium Pyrophosphate, Titanium Dioxide, Sodium Benzoate, Trisodium Phosphate, Sodium Saccharin, Sodium Hydroxide, Methylparaben, Propylparaben

Questions or comments?

call toll free 1-877-274-8358

TOOTHPASTE FOR SENSITIVE TEETH AND CAVITY PREVENTION

FRESH MINT

• FRESHENS BREATH
• STRENGTHENS TEETH WITH ACTIVE FLUORIDE

Compares to the active ingredients in Sensodyne® Extra Whitening*

*This product is not manufactured or distributed by GSK Consumer Healthcare, owner of the registered trademark Sensodyne®.

DESIGNED IN U.S.A. • MADE IN INDIA

Brush Buddies®
WWW.BRUSHBUDDIES.COM

QUESTIONS OR COMMENTS?
1-877-274-8358 TOLL FREE IN USA
1-909-434-0911 INTERNATIONAL

PATENTS, COPYRIGHTS & TRADEMARKS GRANTED OR PENDING WORLDWIDE

DISTRIBUTED BY ASHTEL STUDIOS INC.
ONTARIO, CALIFORNIA 91761